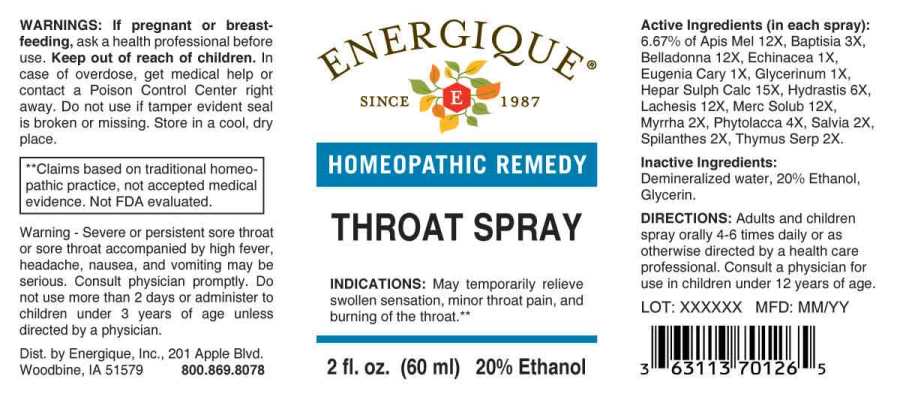 DRUG LABEL: ThroatSpray
NDC: 44911-0450 | Form: SPRAY
Manufacturer: Energique, Inc.
Category: homeopathic | Type: HUMAN OTC DRUG LABEL
Date: 20250516

ACTIVE INGREDIENTS: ECHINACEA ANGUSTIFOLIA WHOLE 1 [hp_X]/1 mL; CLOVE 1 [hp_X]/1 mL; GLYCERIN 1 [hp_X]/1 mL; MYRRH 2 [hp_X]/1 mL; SAGE 2 [hp_X]/1 mL; ACMELLA OLERACEA FLOWERING TOP 2 [hp_X]/1 mL; THYMUS SERPYLLUM WHOLE 2 [hp_X]/1 mL; BAPTISIA TINCTORIA ROOT 3 [hp_X]/1 mL; PHYTOLACCA AMERICANA ROOT 4 [hp_X]/1 mL; GOLDENSEAL 6 [hp_X]/1 mL; APIS MELLIFERA 12 [hp_X]/1 mL; ATROPA BELLADONNA 12 [hp_X]/1 mL; LACHESIS MUTA VENOM 12 [hp_X]/1 mL; MERCURIUS SOLUBILIS 12 [hp_X]/1 mL; CALCIUM SULFIDE 15 [hp_X]/1 mL
INACTIVE INGREDIENTS: WATER; ALCOHOL

DRUG FACTS:

ACTIVE INGREDIENTS:

(in each spray): 6.67% of Echinacea (Angustifolia) 1X, Eugenia Caryophyllata 1X, Glycerinum 1X, Myrrha 2X, Salvia Officinalis 2X, Spilanthes Oleracea 2X, Thymus Serpyllum 2X, Baptisia Tinctoria 3X, Phytolacca Decandra 4X, Hydrastis Canadensis 6X, Apis Mellifica 12X, Belladonna 12X, Lachesis Mutus 12X, Mercurius Solubilis 12X, Hepar Sulphuris Calcareum 15X.

INDICATIONS:

May temporarily relieve swollen sensation, minor throat pain, and burning of the throat.**

**Claims based on traditional homeopathic practice, not accepted medical evidence. Not FDA evaluated.

WARNINGS:

If pregnant or breastfeeding, ask a health professional before use.

Keep out of reach of children. In case of overdose, get medical help or contact a Poison Control Center right away.

Do not use if tamper evident seal is broken or missing.

Store in a cool, dry place.

Warning - Severe or persistent sore throat or sore throat accompanied by high fever, headache, nausea, and vomiting may be serious. Consult physician promptly. Do not use more than 2 days or administer to children under 3 years of age unless directed by physician.

Keep out of reach of children. In case of overdose, get medical help or contact a Poison Control Center right away.

DIRECTIONS:

Adults and children spray orally 4-6 times daily or as otherwise directed by a health care professional. Consult a physician for use in children under 12 years of age.

INDICATIONS:

May temporarily relieve swollen sensation, minor throat pain, and burning of the throat.**

**Claims based on traditional homeopathic practice, not accepted medical evidence. Not FDA evaluated.

INACTIVE INGREDIENTS:

Demineralized Water, 20% Ethanol, Glycerin.

QUESTIONS:

Dist. by Energique, Inc.

201 Apple Blvd.

Woodbine, IA 51579 800.869.8078

PACKAGE LABEL DISPLAY:

ENERGIQUE

SINCE 1987

HOMEOPATHIC REMEDY

THROAT

SPRAY

2 fl. oz. (60 ml)